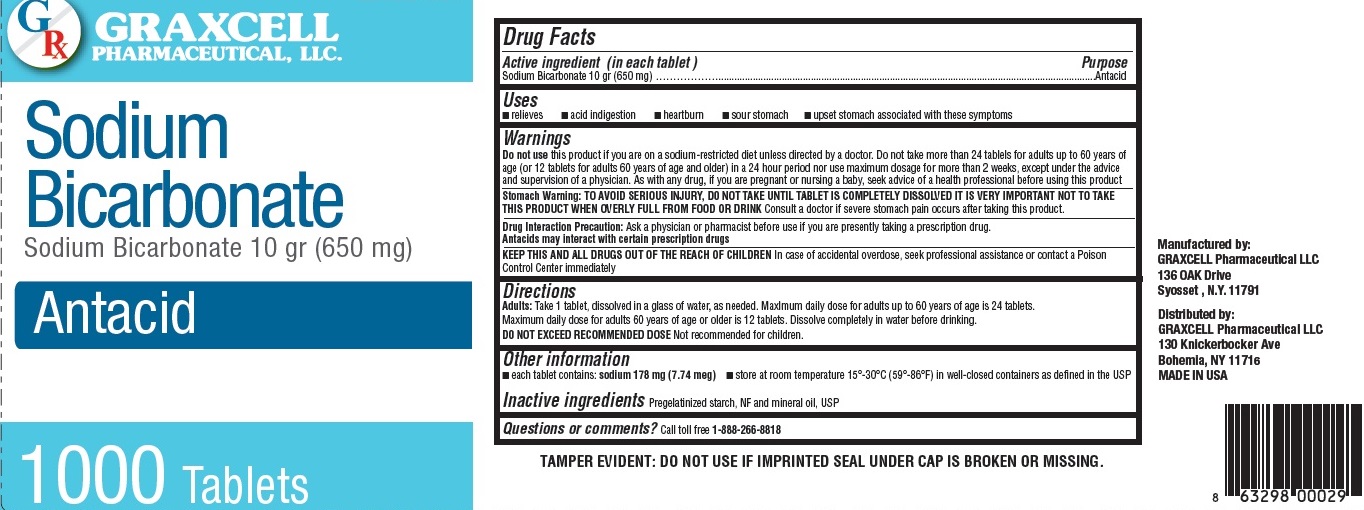 DRUG LABEL: Sodium Bicarbonate 10 gr
NDC: 70795-1190 | Form: TABLET
Manufacturer: GRAXCELL PHARMACEUTICAL, LLC
Category: otc | Type: HUMAN OTC DRUG LABEL
Date: 20251225

ACTIVE INGREDIENTS: SODIUM BICARBONATE 650 mg/1 1
INACTIVE INGREDIENTS: STARCH, CORN; MINERAL OIL

Sodium Bicarbonate 10 gr (650 mg), 70795-1190

Active ingredient (in each tablet)

Sodium bicarbonate 10 gr (650 mg)

Purpose

Antacid

Uses

Relieves

- acid indigestion
- heartburn
- sour stomach
- upset stomach associated with these symptoms

Warnings

Do not use

- this product if you are on a sodium-restricted diet unless directed by a doctor
- Do not take more than 24 tablets for adults up to 60 years of age (or 12 tablets for adults 60 years of age or older) in a 24 hour period nor use maximum dosage for more than 2 weeks, except under the advice and supervision of a physician.
- As with any drug, if you are pregnant or nursing a baby, seek advice of a health professional before using this product

Stomach Warning

- TO AVOID SERIOUS INJURY, D0 NOT TAKE UNTIL TABLET IS COMPLETELY DISSOLVED IT IS VERY IMPORTANT NOT TO TAKE THIS PRODUCT WHEN OVERLY FULL FROM FOOD OR DRINK
- Consult a doctor if severe stomach pain occurs after taking this product.

Drug Interaction Precaution

- Ask a physician or pharmacist before use if you are presently taking a prescription drug
- Antacids may interact with certain prescription drugs

KEEP THIS AND ALL DRUGS OUT OF THE REACH OF CHILDREN

In case of accidental overdose, seek professional assistance or contact a Poison Control Center immediately

Directions

Adults: Take 1 tablet, dissolved in a glass of water, as needed. Maxlmum daily dose for adults up to 60 years of age is 24 tablets.

Maximum daily dose for adults 60 years of age or older is 12 tablets. Dissolve completely in water before drinking.

D0 NOT EXCEED RECOMMENDED DOSE

Not recommended for children.

Other information

- each tablet contains : sodium 178 mg (7.74 meg)
- store at room temperature 15°-30°C (59°-86°F) in well-closed containers as defined in the USP

Inactive ingredients

Pregelatinized starch, NF and mineral oil, USP

Questions or comments?

Call toll free 1-888-266-8818

TAMPER EVIDENT: DO NOT USE IF IMPRINTED SAFETY SEAL UNDER CAP IS BROKEN OR MISSING